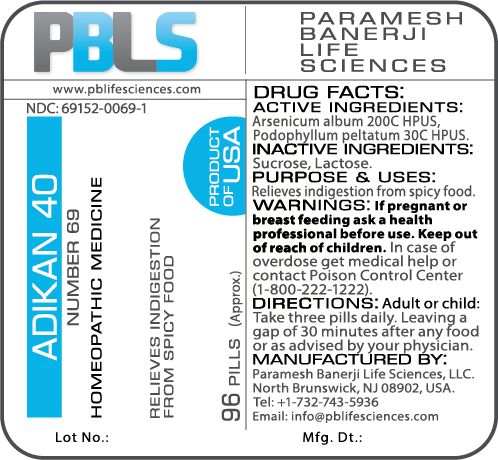 DRUG LABEL: Adikan 40 (Number 69)
NDC: 69152-0069 | Form: PELLET
Manufacturer: Paramesh Banerji Life Sciences LLC
Category: homeopathic | Type: HUMAN OTC DRUG LABEL
Date: 20180117

ACTIVE INGREDIENTS: PODOPHYLLUM 30 [hp_C]/1 1; ARSENIC TRIOXIDE 200 [hp_C]/1 1
INACTIVE INGREDIENTS: SUCROSE; LACTOSE

DRUG FACTS: Active Ingredients

Arsenicum album 200C HPUS, Podophyllum peltatum 30C HPUS

Inactive Ingredients

Sucrose, Lactose

Purpose

Relieves indigestion from spicy food

Uses

Relieves indigestion from spicy food

Warning

If pregnant or breast feeding ask a health professional before use.

Keep out of reach of children. In case of overdose, get medical help or contact a Poison Control Center (1-800-222-1222) right away.

Directions

Adult or child: Take three pills daily. Leaving a gap of 30 minutes after any food or as advised by your physician.

Manufactured By

Paramesh Banerji Life Sciences, LLC.
North Brunswick, NJ 08902, USA.
Tel: +1-732-743-5936

Email: info@pblifesciences.com

Principal Display Panel

NDC: 69152-0069-1

Adikan 40

Number 69

Homeopathic Medicine

Relieves indigestion from spicy food

96 Pills (Approx.)

Product of USA